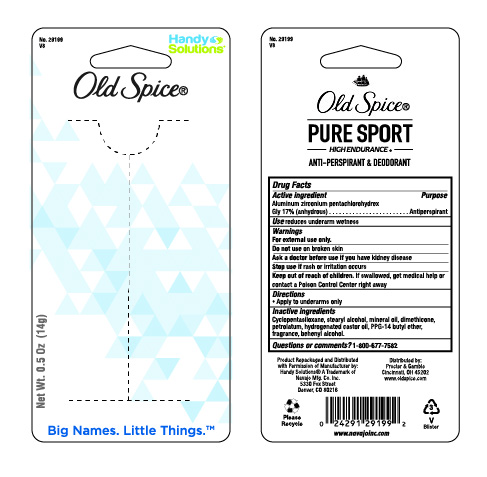 DRUG LABEL: Old Spice
NDC: 67751-187 | Form: STICK
Manufacturer: Navajo Manufacturing Company Inc.
Category: otc | Type: HUMAN OTC DRUG LABEL
Date: 20241002

ACTIVE INGREDIENTS: ALUMINUM ZIRCONIUM TRICHLOROHYDREX GLY 17 g/100 g
INACTIVE INGREDIENTS: CYCLOMETHICONE 5; STEARYL ALCOHOL; MINERAL OIL; DIMETHICONE; PETROLATUM; HYDROGENATED CASTOR OIL; PPG-14 BUTYL ETHER; DOCOSANOL

Old Spice

Active ingredient

Aluminum zirconium pentachlorohydrex Gly 17% (anhydrous)

Purpose

Antiperspirant

Uses

reduces underarm wetness

Warnings

For external use only.

Do not use

on broken skin

Ask a doctor before use

if you have kidney disease

Stop use if

rash or irritation occurs

Keep out of reach of children.

If swallowed, get medical help or contact a Poison Control Center right away.

Directions

- Apply to underarms only

Inactive ingredients

cyclopentasiloxane, stearyl alcohol, mineral oil, dimethicone, petrolatum, hydrogenated castor oil, PPG-14 butyl ether, fragrance, behenyl alcohol.

Questions or comments?

1-800-677-7582